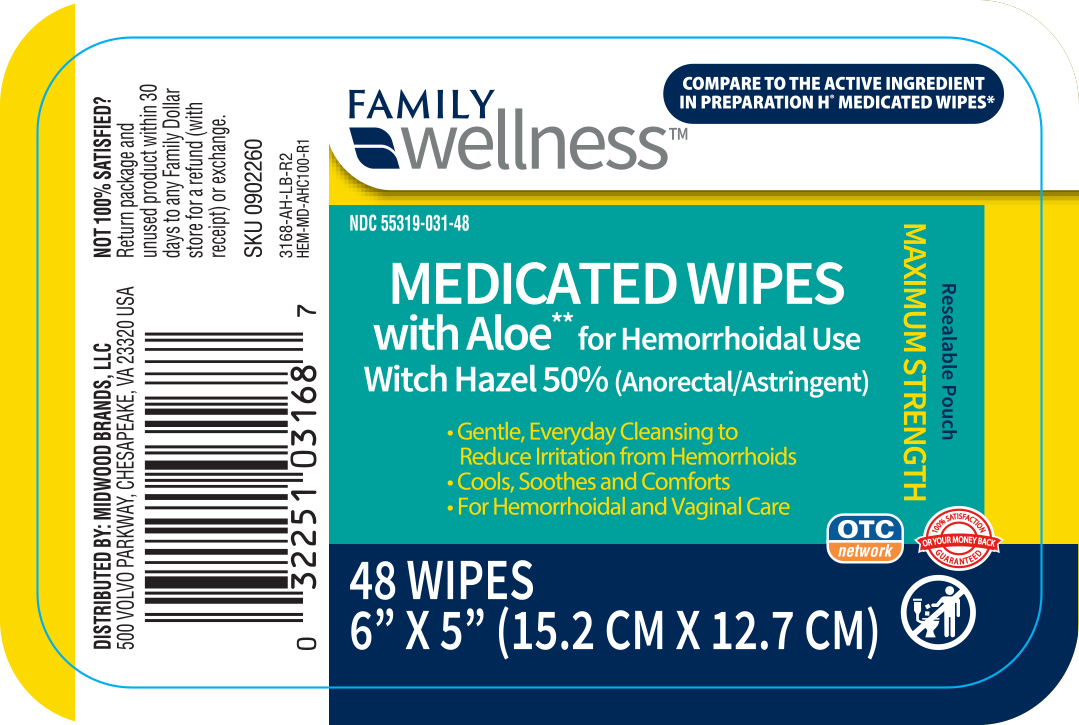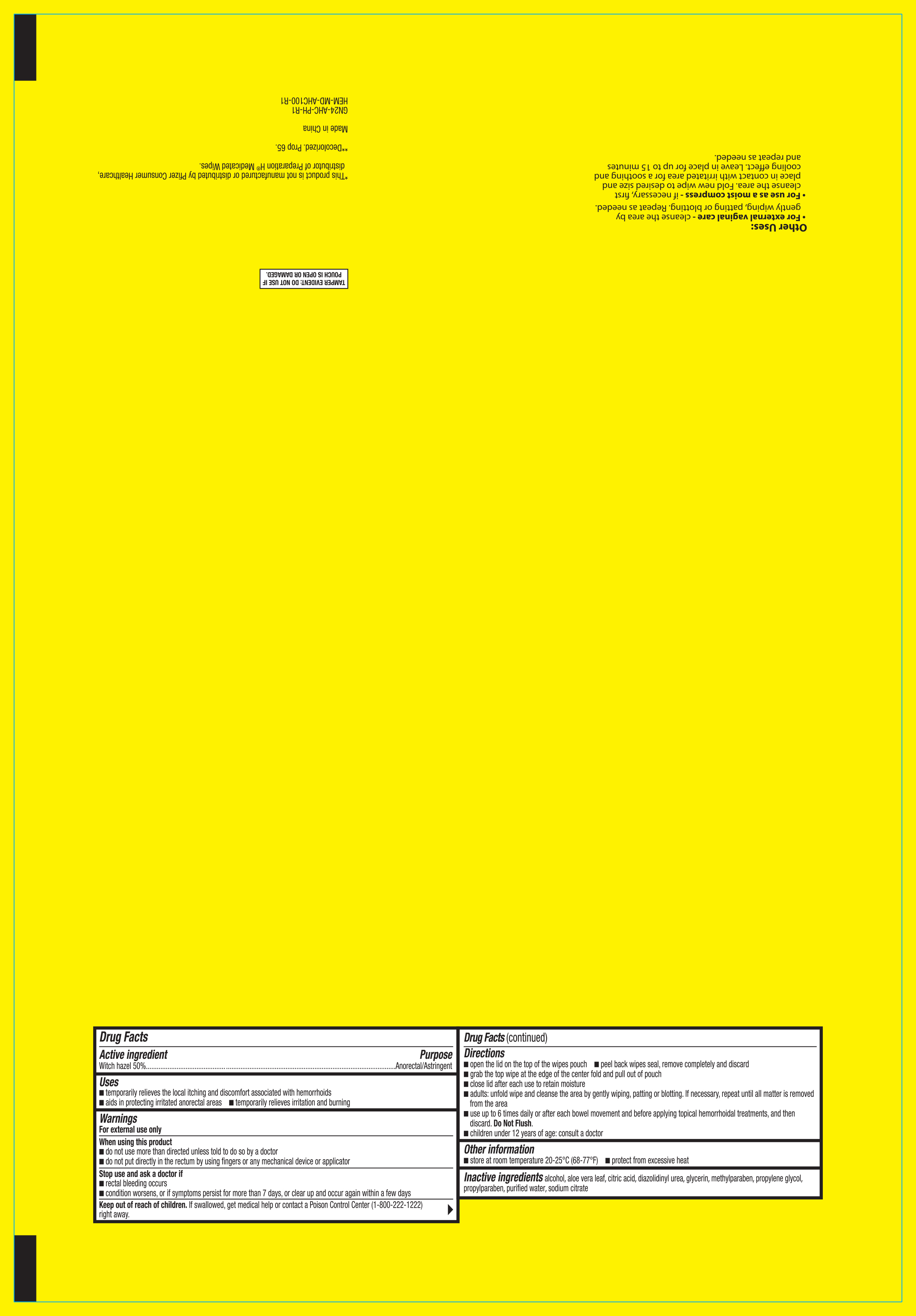 DRUG LABEL: FAMILY WELLNESS MEDICATED WIPES
NDC: 55319-031 | Form: SOLUTION
Manufacturer: FAMILY DOLLAR
Category: otc | Type: HUMAN OTC DRUG LABEL
Date: 20211203

ACTIVE INGREDIENTS: WITCH HAZEL 5 g/1 1
INACTIVE INGREDIENTS: CITRIC ACID MONOHYDRATE; ALOE VERA LEAF; ALCOHOL; DIAZOLIDINYL UREA; GLYCERIN; METHYLPARABEN; PROPYLENE GLYCOL; PROPYLPARABEN; SODIUM CITRATE; WATER

Family Wellness Medicated Wipes 48ct 3168, 2022

Active ingredient Purpose

Witch hazel, 50%...............................................................Anorectal/Astringent

Uses

temporarily relieves the local itching and discomfort associated with hemorrhoids

aids in protecting irritated anorectal areas

temporarily relieves irritation and burning

Warnings

For external use only

When using this product

- do not use more than directed unless told to do so by a doctor
- do not put directly in the rectum by using fingers or any mechanical device or applicator

Stop use and ask a doctor if

- rectal bleeding occurs
- condition worsens, or if symptoms persist for more than 7 days, or clear up and occur again within a few days

Keep out of reach of children. If swallowed, get medical help or contact a Poison Control Center (1-800-222-1222) right away.

Directions

- open the lid on top of the wipes pouch
- peel back wipes seal, remove completely and discard
- grab the top wipe at the edge of the center fold and pull out of pouch
- close lid after each use to retain moisture
- adults: unfold wipe and cleanse the area by gently wiping, patting or blotting. If necessary, repeat until all matter is removed from the area
- use up to 6 times daily or after each bowel movement and before applying topical hemorrhoidal treatments, and then discard. Do Not Flush.
- children under 12 years of age: consult a doctor

Other information

Store at room temperature 20-25°C (68-77°F)

protect from excessive heat

Inactive ingredients

alcohol, aloe vera leaf, citric acid, diazolidinyl urea, glycerin, methylparaben, propylene glycol, propylparaben, purified water, sodium citrate

DOSAGE AND ADMINISTRATION

DISTRIBUTED BY:

FAMILY DOLLAR SERVICES, INC.

10401 MONROE RD.

MATTHEWS, NC 28105 USA

Made in China